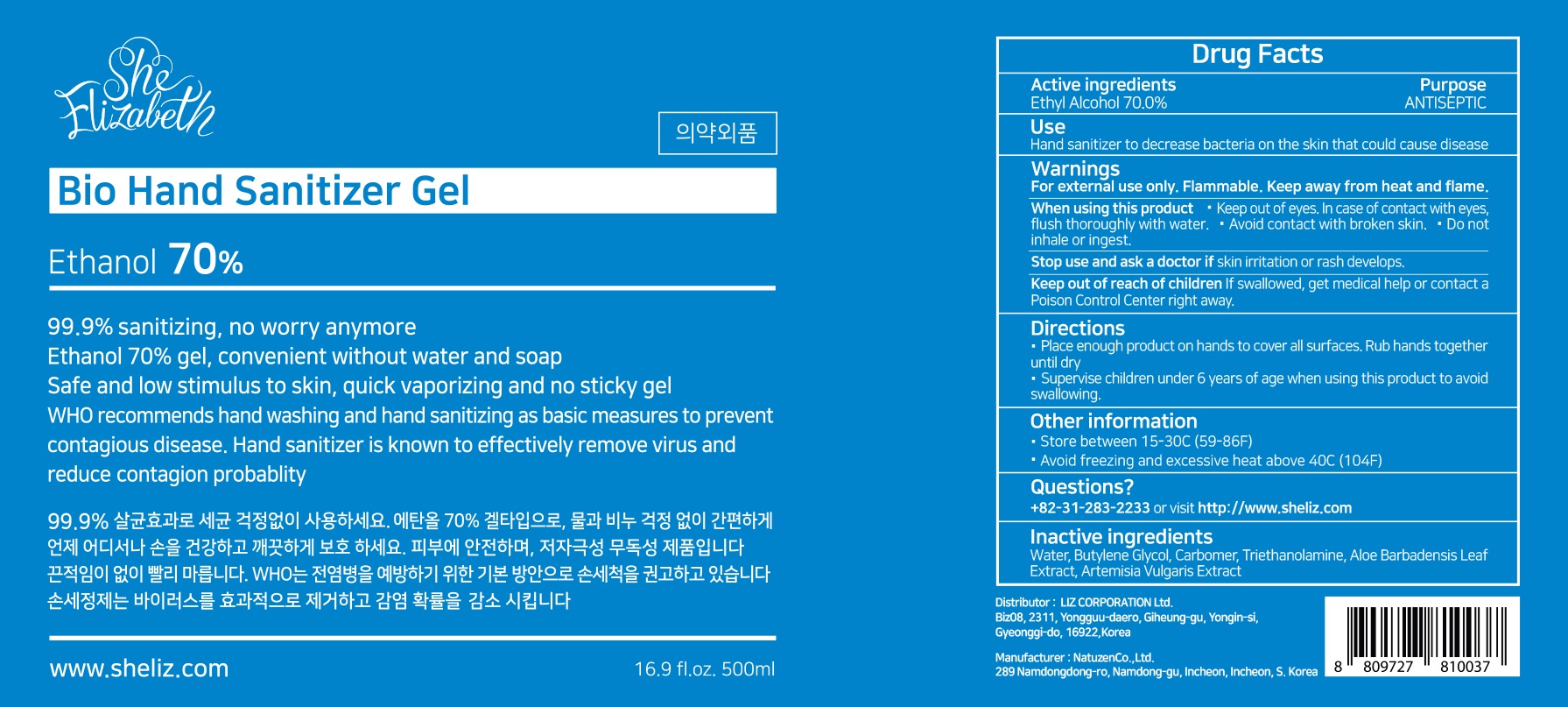 DRUG LABEL: SHE ELIZABETH BIO HAND SANITIZER
NDC: 79487-010 | Form: GEL
Manufacturer: Liz Corporation Ltd
Category: otc | Type: HUMAN OTC DRUG LABEL
Date: 20200709

ACTIVE INGREDIENTS: Alcohol 350 mL/500 mL
INACTIVE INGREDIENTS: Water; Butylene Glycol; CARBOMER HOMOPOLYMER, UNSPECIFIED TYPE; TROLAMINE; ALOE VERA LEAF; ARTEMISIA VULGARIS ROOT

ACTIVE INGREDIENT

Alcohol 70%

INACTIVE INGREDIENTS

Water, Butylene Glycol, Carbomer, Triethanolamine, Aloe Barbadensis Leaf Extract, Artemisia Vulgaris Extract

PURPOSE

Antiseptic

WARNINGS

For external use only. Flammable. Keep away from heat and flame.

When using this product■ Keep out of eyes. In case of contact with eyes,
flush thoroughly with water. ■ Avoid contact with broken skin. ■ Do not inhale
or ingest.

Stop use and ask a doctor if skin irritation or rash develops.

KEEP OUT OF REACH OF CHILDREN

If swallowed, get medical help or contact a Poison Control Center right away.

Uses

Hand sanitizer to decrease bacteria on the skin that could cause disease

Directions

■ Place enough product on hands to cover all surfaces. Rub hands together until dry.
■ Supervise children under 6 years of age when using this product to avoid swallowing.

Other information

• Store between 15-30C (59-86F)
• Avoid freezing and excessive heat above 40C (104F)

QUESTIONS?

+82-31-283-2233 or visit http://www.sheliz.com